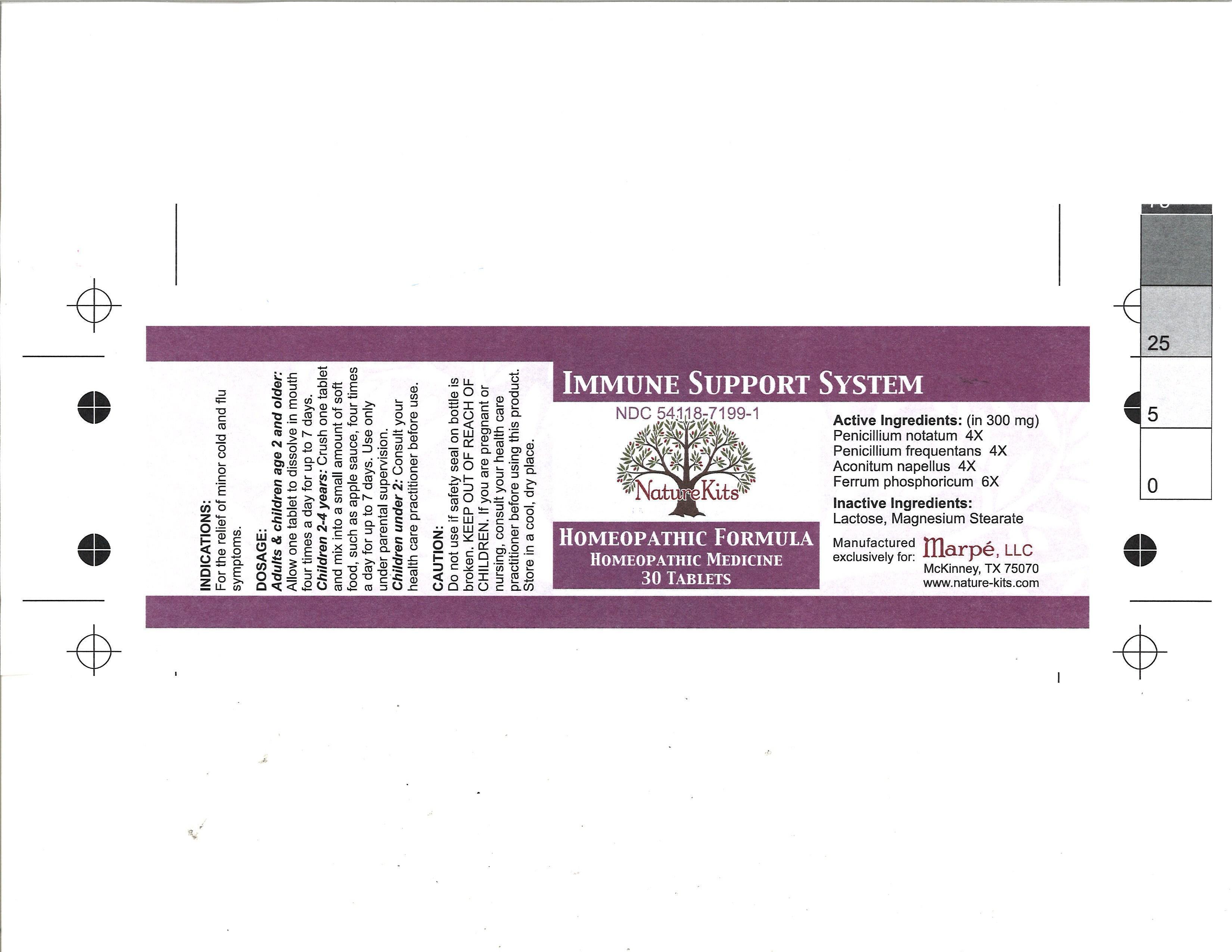 DRUG LABEL: Immune Support System
                
                
NDC: 54118-7199 | Form: TABLET
Manufacturer: ABCO Laboratories, Inc.
Category: homeopathic | Type: HUMAN OTC DRUG LABEL
Date: 20120919

ACTIVE INGREDIENTS: PENICILLIUM CHRYSOGENUM VAR. CHRYSOGENUM 4 [hp_X]/1 1; PENICILLIUM GLABRUM 6 [hp_X]/1 1; ACONITUM NAPELLUS 4 [hp_X]/1 1; FERROSOFERRIC PHOSPHATE 6 [hp_X]/1 1
INACTIVE INGREDIENTS: LACTOSE MONOHYDRATE; MAGNESIUM STEARATE

Immune Support System Tablet

Active Ingredients:

Penicillium Notatum 4X

Penicillium Frequentans 4X

Aconitum Napellus 4X

Ferrum Phosphoricum 6X

PURPOSE

For the relief of minor cold and flu symptoms

Keep out of reach of children.

Indications:

for the relief of minor cold and flu symptoms.

Dosage:

Adults and children age 2 and older: allow one tablet to dissolve in mouth four times a day.

Children 2-4 years: crush one tablet and mix into a small amount of soft food, such as apple sauce, four times a day. use only under parental supervision.

Children under 2 years: consult your health care practitioner before use.

Do not use if safety seal on bottle is broken.

store in a cool, dry place.

Inactive Ingredients:

Lactose, magnesium stearate

DOSAGE AND ADMINISTRATION

Adults and children age 2 and older: allow one tablet to dissolve in mouth four times a day.

Children 2-4 years: crush one tablet and mix into a small amount of soft food, such as apple sauce, four times a day. use only under parental supervision.

Children under 2 years: consult your health care practitioner before use.

Image of bottle label
label.JPEG